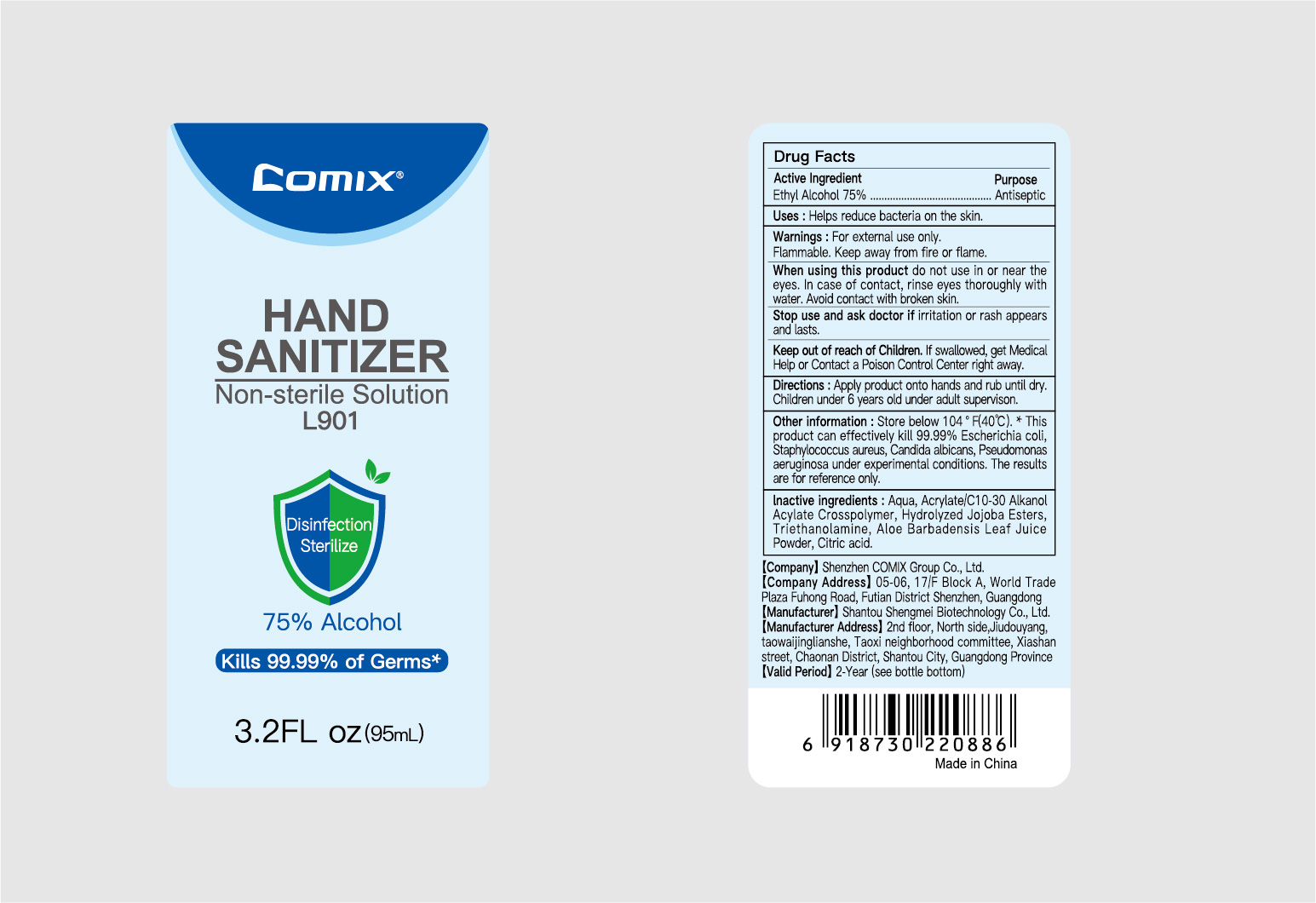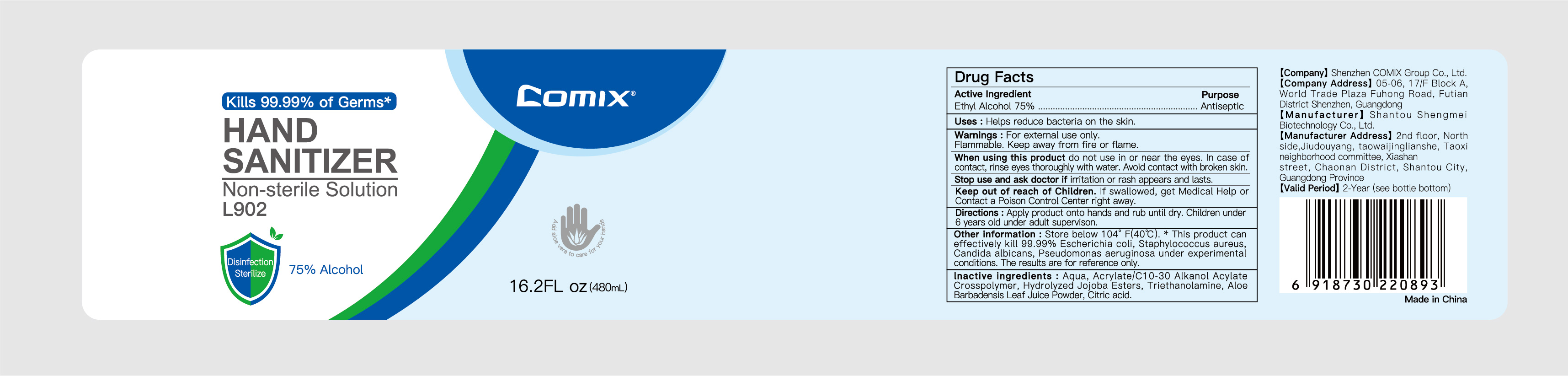 DRUG LABEL: Comix Hand Sanitizer
NDC: 55450-007 | Form: GEL
Manufacturer: Shantou Shengmei Biotechnology Co., Ltd.
Category: otc | Type: HUMAN OTC DRUG LABEL
Date: 20200820

ACTIVE INGREDIENTS: ALCOHOL 75 mL/100 mL
INACTIVE INGREDIENTS: CARBOMER INTERPOLYMER TYPE A (ALLYL SUCROSE CROSSLINKED); HYDROLYZED JOJOBA ESTERS (ACID FORM); TROLAMINE; ALOE VERA LEAF; CITRIC ACID MONOHYDRATE; WATER

Comix Hand Sanitizer

Active ingredient

Alcohol 75% v/v. Purpose: Antiseptic

Purpose

Antiseptic, Hand Sanitizer

Uses

Helps reduce bacteria on the skin

Warnings

For external use only.

Flammable. Keep away from heat or flame.

When using this product

do not use in or near the eyes. In case of contact with eyes, rinse eyes thoroughly with water. Avoid contact with broken skin.

Stop use and ask doctor

if irritation or rash appears and lasts.

Keep out of reach of children

If swallowed, get medical help or contact a poison control center right away.

Directions

Apply product onto hands and rub until dry. Children under 6 years old under adult supervision.

Other information

Store below 105F (40F). * This product can effectively kill 99.99% Escherichia coli, Staphylococcus aureus, Candida albicans, Pseudomonas aeruginosa under experimental conditions. These results are for reference only.

Inactive ingredients

Aqua, Hydrolyzed Jojoba Esters, Acrylates/C10-30 Alkyl Acrylate Crosspolymer, Triethanolamine, Aloe Barbadensis Leaf Juice Powder, Citric Acid

PACKAGE LABEL

55450-007-01 95mL

Comix

HAND SANITIZER

Non-sterile Solution

L901

Disinfection

Sterilize

75% Alcohol

Kills 99.99% of Germs*

3.2 FL oz (95mL)

55450-007-02 480mL

Comix

Kills 99.99% of Germs*

HAND SANITIZER

Non-sterile Solution

L902

Disinfection

Sterilize

75% Alcohol

16.2 FL oz (480mL)